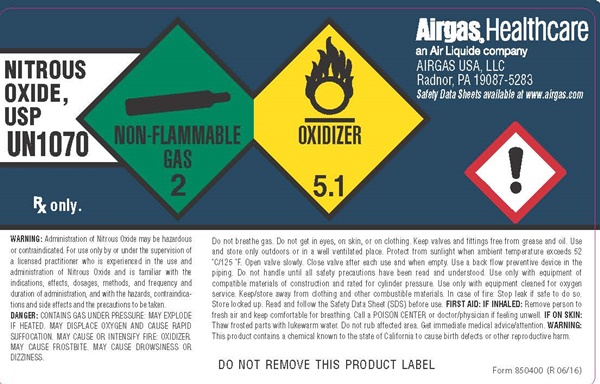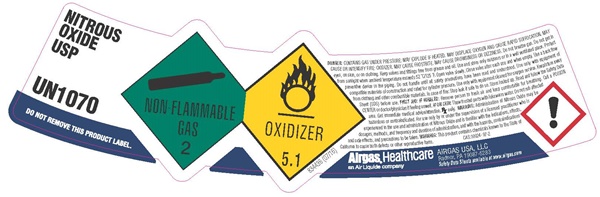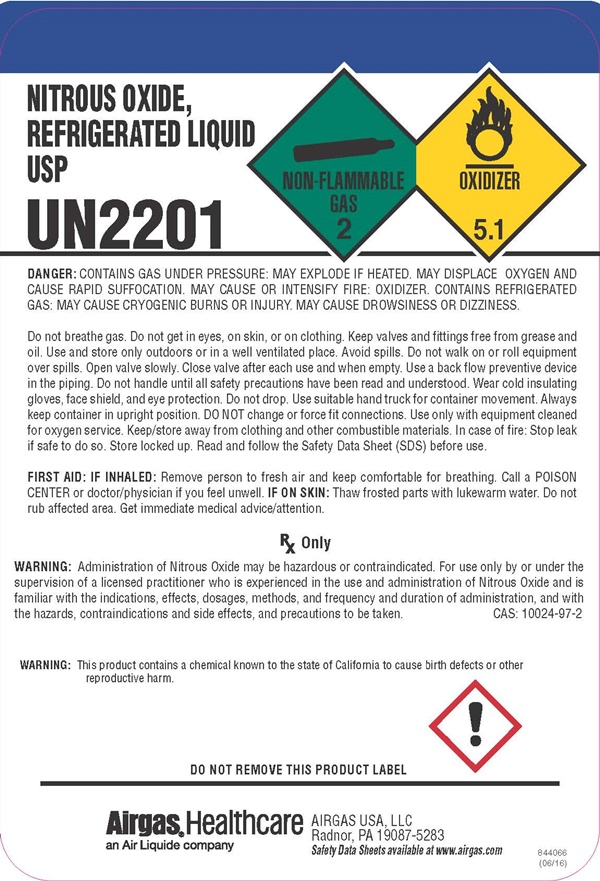 DRUG LABEL: NITROUS OXIDE
NDC: 11054-007 | Form: GAS
Manufacturer: AIRGAS USA, LLC
Category: prescription | Type: HUMAN PRESCRIPTION DRUG LABEL
Date: 20250903

ACTIVE INGREDIENTS: NITROUS OXIDE 992 mL/1 L

Nitrous Oxide, USP - 007

NITROUS OXIDE, REFREGERATED LIQUID USP product label

NITROUS OXIDE,
REFREGERATED LIQUID
USP

UN2201

NON-FLAMMABLE GAS 2 OXIDIZER 5.1

DANGER: CONTAINS GAS UNDER PRESSURE: MAY EXPLODE IF HEATED. MAY DISPLACE OXYGEN AND CAUSE RAPID SUFFICATION. MAY CAUSE OR INTENSIFY FIRE: OXIDIZER. CONTAINS REFRIGERATED GAS: MAY CAUSE CRYOGENIC BURNS OR INJURY. MAY CAUSE DROWSINESS OR DIZZINESS.

Do not breathe gas. Do not get into eyes, on skin, or on clothing. Keep valves and fittings free from grease and oil. Use and store only outdoors or in a well ventilated place. Avoid spills. Do not walk or roll equipment over spills. Open valve slowly. Close valve after each use and when empty. Use a back flow preventive device in the piping. Do not handle until all safety precautions have been read and understood. Wear cold insulating gloves/face shield/eye protection. Do not drop. Use a suitable hand truck for container movement. Always keep container in upright position. DO NOT change or force fit connections. Use only with equipment cleaned for oxygen service. Keep/store away from clothing and other combustible materials. In case of fire: Stop leak if safe to do so. Store locked up. Read and follow the Safety Data Sheet (SDS) before use.

FIRST AID: IF INHALED: Remove to fresh air and keep comfortable for breathing. Get medical advice/attention. IF ON SKIN: Thaw frosted parts with lukewarm water. Do not rub affected area. Call a POISON CENTER or doctor/physician if feeling unwell.

RX Only

WARNING: Administration of Nitrous Oxide may be hazardous or contraindicated. For use only by or under the supervision of a licensed practitioner who is experienced in the use and administration of Nitrous Oxide and is familiar with the indications, effects, dosages, methods, and frequency and duration of administration, and with the hazards, contraindications and side effects, and precautions to be taken.
CAS: 10024-97-2

WARNING: This product contains a chemical known to the state of California to cause birth defects or other reproductive harm.

DO NOT REMOVE THIS PRODUCT LABEL

AIRGAS® Healthcare
an Air Liquide Company
AIRGAS USA, LLC
Radnor, PA 19087-5283

Safety Data Sheets available at www.airgas.com

844066 (06/16)

NITROUS OXIDE, USP product label

NITROUS OXIDE,
USP
UN1070

NON-FLAMMABLE GAS 2 OXIDIZER 5.1

Rx only.

WARNING: Administration of Nitrous Oxide may be hazardous or contraindicated. For use only by or under the supervision of a licensed practitioner who is experienced in the use and administration of Nitrous Oxide and is familiar with the indications, effects, dosages, methods, and frequency and duration of administration, and with the hazards, contraindications and side effects and precautions to be taken.

DANGER: CONTAINS GAS UNDER PRESSURE: MAY EXPLODE IF HEATED. MAY DISPLACE OXYGEN AND CAUSE RAPID SUFFICATION. MAY CAUSE OR INTENSIFY FIRE: OXIDIZER. MAY CAUSE FROSTBITE. MAY CAUSE DROWSINESS OR DIZZINESS.

Do not breathe gas. Do not get into eyes, on skin, or on clothing. Keep valves and fittings free from grease and oil. Use and store only outdoors or in a well ventilated place. Protect from sunlight when the ambient temperature exceeds 52°C/125°F. Open valve slowly. Close valve after each use and when empty. Use a back flow preventive device in the piping. Do not handle until all safety precautions have been read and understood. Use only with equipment of compatible materials of construction and rated for cylinder pressure. Use only with equipment cleaned for oxygen service. Keep/store away from clothing and other combustible materials. In case of fire: Stop leak if safe to do so. Store locked up. Read and follow the Safety Data Sheet (SDS) before use. FIRST AID: IF INHALED: Remove to fresh air and keep comfortable for breathing. Call a POISON CENTER or doctor/physician if feeling unwell. IF ON SKIN: Thaw frosted parts with lukewarm water. Do not rub affected area. Get immediate medical advice/attention. WARNING: This product contains a chemical known to the state of California to cause birth defects or other reproductive harm.

DO NOT REMOVE THIS PRODUCT LABEL

Form 850400 (R 06/16)

AIRGAS® Healthcare
an Air Liquide Company
AIRGAS USA, LLC
Radnor, PA 19087-5283

Safety Data Sheets available at www.airgas.com

NITROUS OXIDE USP product label

NITROUS OXIDE
USP

UN1070

DO NOT REMOVE THIS PRODUCT LABEL

NON-FLAMMABLE GAS 2 OXIDIZR 5.1

834436 (07/16)

DANGER: CONTAINS GAS UNDER PRESSURE: MAY EXPLODE IF HEATED. MAY DISPLACE OXYGEN AND CAUSE RAPID SUFFICATION. MAY CAUSE OR INTENSIFY FIRE: OXIDIZER. MAY CAUSE FROSTBITE. MAY CAUSE DROWSINESS OR DIZZINESS. Do not breathe gas. Do not get into eyes, on skin, or on clothing. Keep valves and fittings free from grease and oil. Use and store only outdoors or in a well ventilated place. Protect from sunlight when the ambient temperature exceeds 52°C/125°F. Open valve slowly. Close valve after each use and when empty. Use a back flow preventive device in the piping. Do not handle until all safety precautions have been read and understood. Use only with equipment of compatible materials of construction and rated for cylinder pressure. Use only with equipment cleaned for oxygen service. Keep/store away from clothing and other combustible materials. In case of fire: Stop leak if safe to do so. Store locked up. Read and follow the Safety Data Sheet (SDS) before use. FIRST AID: IF INHALED: Remove to fresh air and keep comfortable for breathing. Call a POISON CENTER or doctor/physician if feeling unwell. IF ON SKIN: Thaw frosted parts with lukewarm water. Do not rub affected area. Get immediate medical advice/attention. Rx only. WARNING: Administration of Nitrous Oxide may be hazardous or contraindicated. For use only by or under the supervision of a licensed practitioner who is experienced in the use and administration of Nitrous Oxide and is familiar with the indications, effects, dosages, methods, and frequency and duration of administration, and with the hazards, contraindications and side effects and precautions to be taken. WARNING: This product contains a chemical known to the state of California to cause birth defects or other reproductive harm.

AIRGAS® Healthcare
an Air Liquide Company
AIRGAS USA, LLC
Radnor, PA 19087-5283

Safety Data Sheets available at www.airgas.com